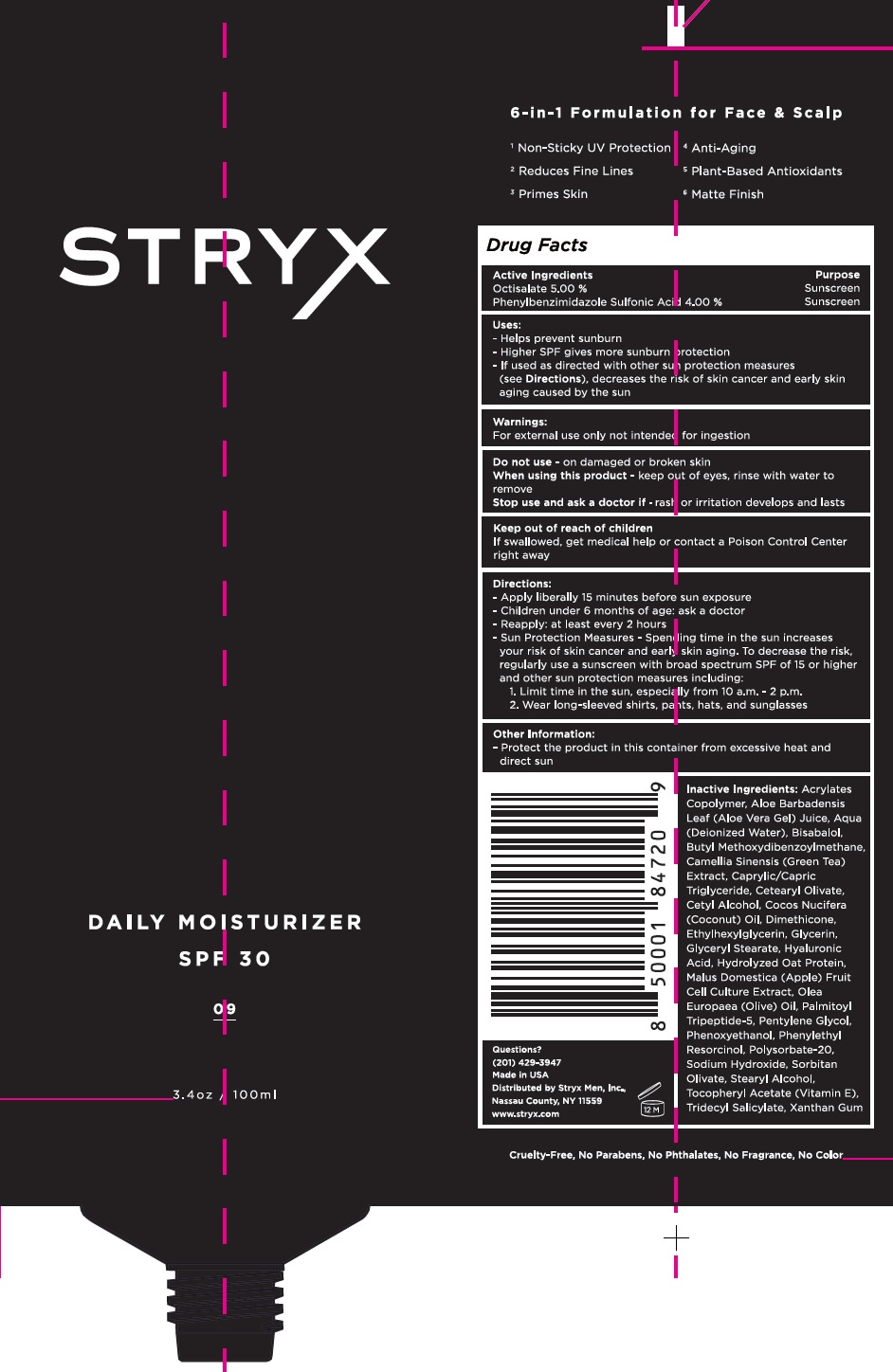 DRUG LABEL: STRYX Daily Moisturizer SPF-30
NDC: 82281-239 | Form: CREAM
Manufacturer: STRYX MEN, INC.
Category: otc | Type: HUMAN OTC DRUG LABEL
Date: 20231111

ACTIVE INGREDIENTS: OCTISALATE 50 mg/1 mL; ENSULIZOLE 40 mg/1 mL
INACTIVE INGREDIENTS: ALOE VERA LEAF; WATER; LEVOMENOL; AVOBENZONE; GREEN TEA LEAF; MEDIUM-CHAIN TRIGLYCERIDES; CETEARYL OLIVATE; CETYL ALCOHOL; COCONUT OIL; DIMETHICONE; ETHYLHEXYLGLYCERIN; GLYCERIN; GLYCERYL MONOSTEARATE; HYALURONIC ACID; APPLE; OLEA EUROPAEA (OLIVE) OIL UNSAPONIFIABLES; PALMITOYL TRIPEPTIDE-5; PENTYLENE GLYCOL; PHENOXYETHANOL; PHENYLETHYL RESORCINOL; POLYSORBATE 20; SODIUM HYDROXIDE; SORBITAN OLIVATE; STEARYL ALCOHOL; .ALPHA.-TOCOPHEROL ACETATE; TRIDECYL SALICYLATE; XANTHAN GUM

STRYX Daily Moisturizer SPF-30

Active Ingredients

Octisalate 5.00%

Phenylbenzimidazole Sulfonic Acid 4.00%

Purpose

Sunscreen

Uses:

- Helps prevent sunburn

- Higher SPF gives more sunburn protection

- If used as directed with other sun protection measures (see Directions), decreases the risk of skin cancer and early skin aging caused by the sun

Warnings:

For external use only not intended for ingestion

Do not use

- on damaged or broken skin

When using this product

- keep out of eyes, rinse with water to remove

Stop use and ask a doctor if

i rash or irritation develops and lasts

Keep out of reach of children

If swallowed, get medical help or contact a Poison Control Center right away

Directions:

- Apply liberally 15 minutes before sun exposure

- Children under 6 months of age: ask a doctor

- Reapply: at least every 2 hours

- Sun Protection Measures- Spending time in the sun increases your risk of skin cancer and early skin aging. To decrease the risk, regularly use a sunscreen with broad spectrum SPF of 15 or higher and other sun protection measures including:

1. Limit time in the sun, especially from 10 a.m.- 2 p.m.
2. Wear long-sleeved shirts, pants, hats, and sunglasses

Other Information:

- Protect the product in this container from excessive heat and direct sun

Inactive Ingredients:

Acrylates Copolymer, Aloe Barbadensis Leaf (Aloe Vera Gel) Juice, Aqua (Deionized Water), Bisabalol, Butyl Methoxydibenzoylmethane, Camellia Sinensis (Green Tea) Extract, Caprylic/Capric Triglyceride, Cetearyl Olivate, Cetyl Alcohol, Cocos Nucifera (Coconut) Oil, Dimethicone, Ethylhexylglycerin, Glycerin, Glyceryl Stearate, Hyaluronic Acid, Hydrolyzed Oat Protein, Malus Domestica (Apple) Fruit Cell Culture Extract, Olea Europaea (Olive) Oil, Palmitoyl Tripeptide-5, Pentylene GLycol, Phenoxyethanol, Phenylethyl Resorcinol, Polysorbate-20, Sodium Hydroxide, Sorbitan Olivate, Stearyl Alcohol, Tocopheryl Acetate (Vitamin E), Tridecyl Salicylate, Xanthan Gum